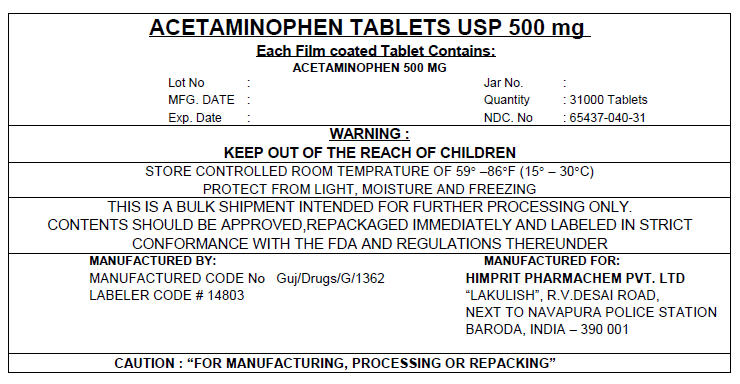 DRUG LABEL: ACETAMINOPHEN
NDC: 65437-040 | Form: TABLET, FILM COATED
Manufacturer: HIMPRIT PHARMACHEM PVT LTD
Category: otc | Type: HUMAN OTC DRUG LABEL
Date: 20100720

ACTIVE INGREDIENTS: ACETAMINOPHEN 500 mg/1 1
INACTIVE INGREDIENTS: SODIUM METABISULFITE; SILICON DIOXIDE; CELLULOSE, MICROCRYSTALLINE; CROSCARMELLOSE SODIUM; POLYETHYLENE GLYCOL; STEARIC ACID; TITANIUM DIOXIDE; WATER

ACETAINOPHEN TABLETS USP 500 mg

Drug Facts

Active ingredients (in each Caplet)

Acetaminophen 500 mg

Purpose

Pain reliever/ fever reducer

Uses

Temporarily relieves minor aches and pains due to :

- headache
- backache
- the common cold
- menstrual cramps

- muscular aches
- arthritis
- toothache
- reduces fever

Warnings

Overdose Warning

Taking more than the recommended dose can cause serious health problems, including liver damage. In case of overdose, get medical help or contact a Poison Control Center right away. Quick medical attention is critical for adults as well as for children even you do not notice any signs or symptoms.

Alcohol Warnings

If you consume 3 or more alcoholic drinks every day, ask your doctor if you should take acetaminophen or other pain relievers/fever reducers. Acetaminophen may cause liver damage.

Do not use

- with any other product containing acetaminophen

Stop use and Ask a doctor if

- fever gets worse or lasts for more than 3 days
- redness or swelling is present
- pain gets worse or lasts for more than 10 days
- new symptoms occur

PREGNANCY OR BREAST FEEDING

If pregnant or breast-feeding, ask a health professional before use

Keep out of reach of children.

Direction

- do not use more that directed (see overdose warning)
- adults and children 12 years and over : take 2 caplets every 6 hours as needed
- do not take more than 8 caplets in 24 hours
- Children under 12 years : do not use this adult Extra Strength product in children under 12 years of age; this will provide more than the recommended dose (overdose) and could cause serious health problems.

Other information

- Store at room temperature

Inactive ingredients

croscarmellose sodium, hypromellose, polythlene glycol,sodium metabisulfate, stearic acid,, sodium starch glycolate

PRINCIPAL DISPLAY PANEL - 500 mg Tablet Shipper Label

ACETAMINOPHEN TABLETS USP 500 mg
Each Film coated Tablet Contains:
ACETAMINOPHEN 500 MG

Lot No :
MFG. DATE :
Exp. Date :
Jar No. :
Quantity : 31000 Tablets
NDC. No : 65437-040-31

WARNING :
KEEP OUT OF THE REACH OF CHILDREN

STORE CONTROLLED ROOM TEMPRATURE OF 59° –86°F (15° – 30°C)
PROTECT FROM LIGHT, MOISTURE AND FREEZING

THIS IS A BULK SHIPMENT INTENDED FOR FURTHER PROCESSING ONLY.
CONTENTS SHOULD BE APPROVED,REPACKAGED IMMEDIATELY AND LABELED IN STRICT
CONFORMANCE WITH THE FDA AND REGULATIONS THEREUNDER

MANUFACTURED BY:
MANUFACTURED CODE No Guj/Drugs/G/1362
LABELER CODE # 14803

MANUFACTURED FOR:
HIMPRIT PHARMACHEM PVT. LTD
"LAKULISH", R.V.DESAI ROAD,
NEXT TO NAVAPURA POLICE STATION
BARODA, INDIA – 390 001

CAUTION : "FOR MANUFACTURING, PROCESSING OR REPACKING"